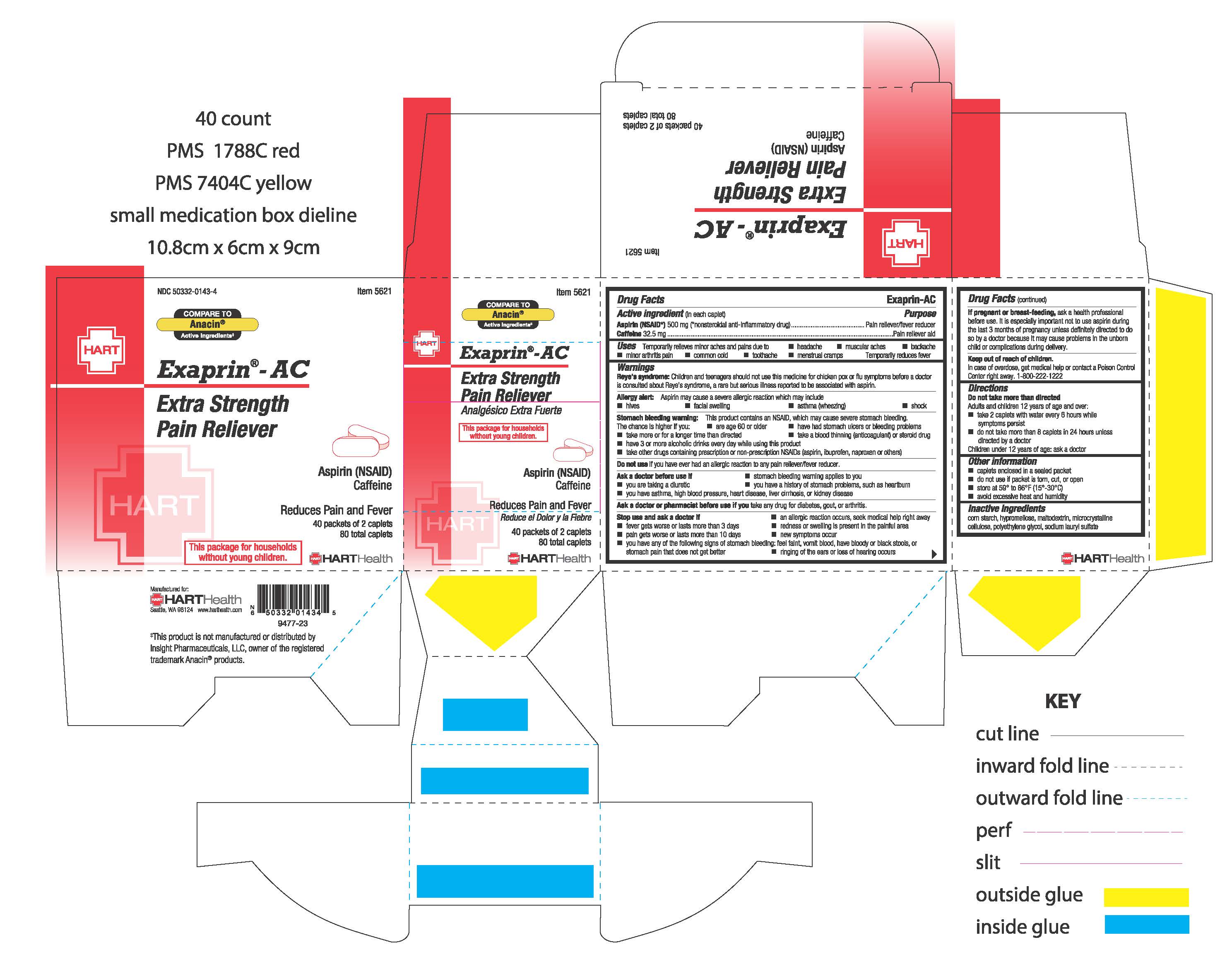 DRUG LABEL: EXAPRIN-AC
NDC: 50332-0143 | Form: TABLET, FILM COATED
Manufacturer: HART Health
Category: otc | Type: HUMAN OTC DRUG LABEL
Date: 20241204

ACTIVE INGREDIENTS: ASPIRIN 500 mg/1 1; CAFFEINE 32.5 mg/1 1
INACTIVE INGREDIENTS: STARCH, CORN; HYPROMELLOSE, UNSPECIFIED; MALTODEXTRIN; POLYETHYLENE GLYCOL, UNSPECIFIED; MICROCRYSTALLINE CELLULOSE; SODIUM LAURYL SULFATE

EXAPRIN-AC

Active ingredients (in each caplet)

Aspirin (NSAID*) 500 mg *nonsteroidal anti-inflammatory drug

Caffeine 32.5 mg

Purpose

Pain reliever/fever reducer

Pain reliever aid

Uses
for the temporary relief of minor aches and pains due to
■ headache

■ muscular aches

■ backache pain

■ minor arthritis pain

■ common cold

■ toothache

■ menstrual cramps

Temporarily reduces fever

Warnings

Reye's syndrome:

Children and teenagers should not use this medicine for chicken pox or flu symptoms before a doctor is consulted about Reye's Syndrome, a rare but serious illness reported to be associated with salicylates.

Allergy alert:

Magnesium salicylate may cause a severe allergic reaction which may include:

■ hives

■ facial swelling

■ asthma (wheezing)

■ shock

Stomach bleeding warning:

This product contains an NSAID, which may cause severe stomach bleeding. The chance is higher if you:

■ are age 60 or older

■ have had stomach ulcers or bleeding problems

■ take a blood thinning (anticoagulant) or steroid drug

■ take other drugs containing prescription or nonprescription NSAIDs (aspirin, ibuprofen, naproxen, or others)

■ have 3 or more alcoholic drinks every day while using this product

■ take more or for a longer time than directed

Do not use if you have ever had an allergic reaction to any pain reliever/fever reducer.

Ask a doctor before use if

■ stomach bleeding warning applies to you

■ you have a history of stomach problems, such as heartburn

■ you have asthma, high blood pressure, heart disease, liver cirrhosis, or kidney disease

■ you are taking a diuretic

Ask a doctor or pharmacist before use if you take any drug for diabetes, gout or arthritis

Stop use and ask a doctor if

■ an allergic reaction occurs, seek medical help right away

■ fever worsens or lasts more than 3 days

■ pain worsens or lasts more than 10 days

■ you have any of the following signs of stomach bleeding: feel faint, vomit blood, have bloody or black stools, or stomach pain that does not get better

■ ringing in the ears or loss of hearing occurs

■ new symptoms occur

■ redness or swelling is present

These could be signs of a serious condition.

PREGNANCY OR BREAST FEEDING

If pregnant or breast-feeding, ask a health professional before use. It is especially important not to use aspirin at 20 weeks or later in pregnancy unless definitely directed to do so by a doctor because it may cause problems in the unborn child or complications during delivery.

Keep out of reach of children. In case of overdose, get medical help or contact a Poison Control Center right away. 1-800-222-1222

Directions

Do not take more than directed.

Adults and children 12 years of age and over:

■ take 2 caplets with a full glass of water every 6 hours while symptoms persist

■ do not take more than 8 caplets in 24 hours unless directed by a doctor

Children under 12 years: ask a doctor

Other information

■ caplets enclosed in a sealed packet

■ do not use if packet is torn, cut or open

■ store at 59° to 86°F (15°-30°C)

■ avoid excessive heat and humidity

Inactive ingredients

corn starch, hypromellose, maltodextrin, microcrystalline cellulose, polyethylene glycol, sodium lauryl sulfate